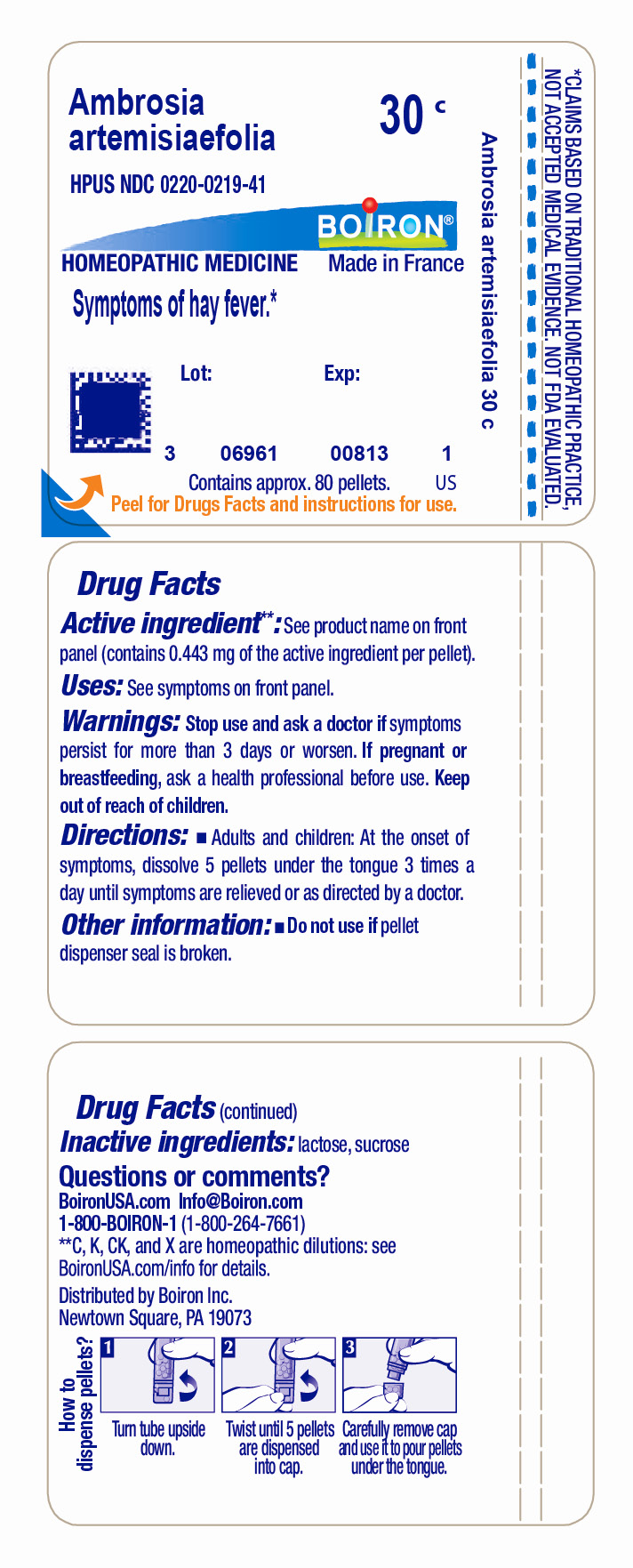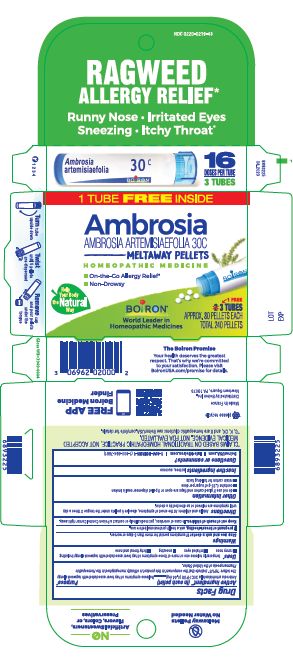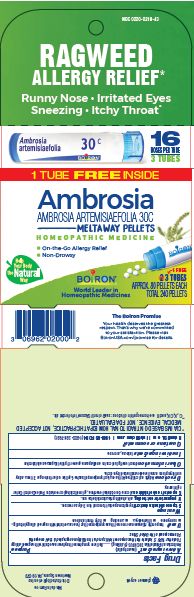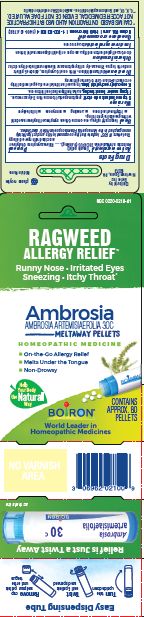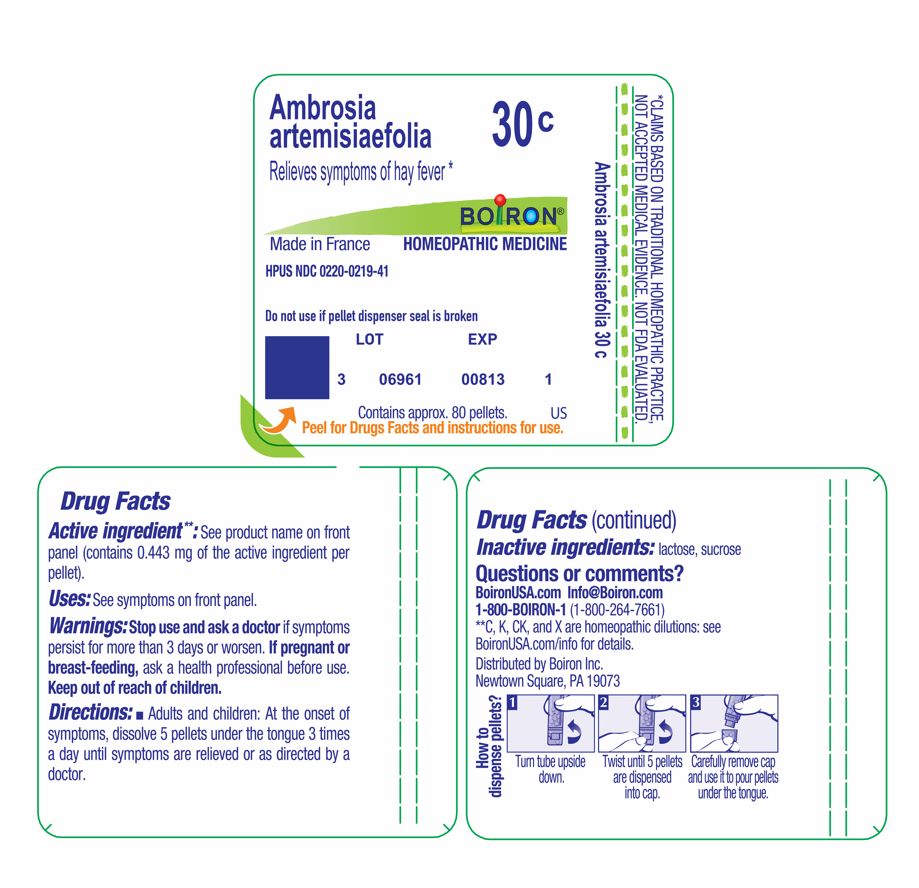 DRUG LABEL: Ambrosia artemisiaefolia
NDC: 0220-0219 | Form: PELLET
Manufacturer: Boiron
Category: homeopathic | Type: HUMAN OTC DRUG LABEL
Date: 20240208

ACTIVE INGREDIENTS: AMBROSIA ARTEMISIIFOLIA 30 [hp_C]/30 [hp_C]
INACTIVE INGREDIENTS: LACTOSE, UNSPECIFIED FORM; SUCROSE

Ambrosia artemisiaefolia 30C

Active ingredients**

Ambrosia artemisiaefolia 30C HPUS (0.44 mg)

The letters "HPUS" indicate that the components in this product are officially monographed in the Homeopathic Pharmacopoeia of the United States.

Uses*

temporarily relieves one or more of these symptoms of hay fever associated with ragweed allergy including:

- runny nose
- irritated eyes
- sneezing
- itchy throat and nose

INDICATIONS AND USAGE

Box Purpose*

Relieves symptoms of hay fever associated with ragweed allergy

Tube Purpose

Relieves symptoms of hay fever*

Stop use and ask a doctor if symptoms persist for more than 3 days or worsen.

PREGNANCY OR BREAST FEEDING

If pregnant or breast-feeding, ask a health professional before use

Keep out of reach of children. In case of accidental overdose, get medical help or contact a Poison Control Center right away.

Ragweed Allergy Relief*

On-the-Go Allergy Relief*

Non-Drowsy

3 Tubes

Approx. 80 Pellets Each

Total 240 Pellets

16 Doses per tube

do not use if glued carton end flaps are open or if pellet dispenser seal is broken

contains 0.25 g of sugar per dose

retain carton for full drug facts

How to dispense pellets? Turn tube upside down. Twist until 5 pellets are dispensed into cap. Carefully remove the cap and use it to pour pellets under the tongue.
*CLAIMS BASED ON TRADITIONAL HOMEOPATHIC PRACTICE NOT ACCEPTED MEDICAL EVIDENCE. NOT FDA EVALUATED.
*C,K,CK, and X are homeopathic dilutions: see BoironUSA.com/info for details.

INACTIVE INGREDIENT

lactose, sucrose

Directions

Adults and children: At the onset of symptoms, dissolve 5 pellets under the tongue 3 times a day until symptoms are relieved or as directed by a doctor.

QUESTIONS

1-800-BOIRON-1 (1-800-264-7661),
BoironUSA.com Info@boiron.com
Distributed by Boiron, Inc. Newtown Square, PA 19073